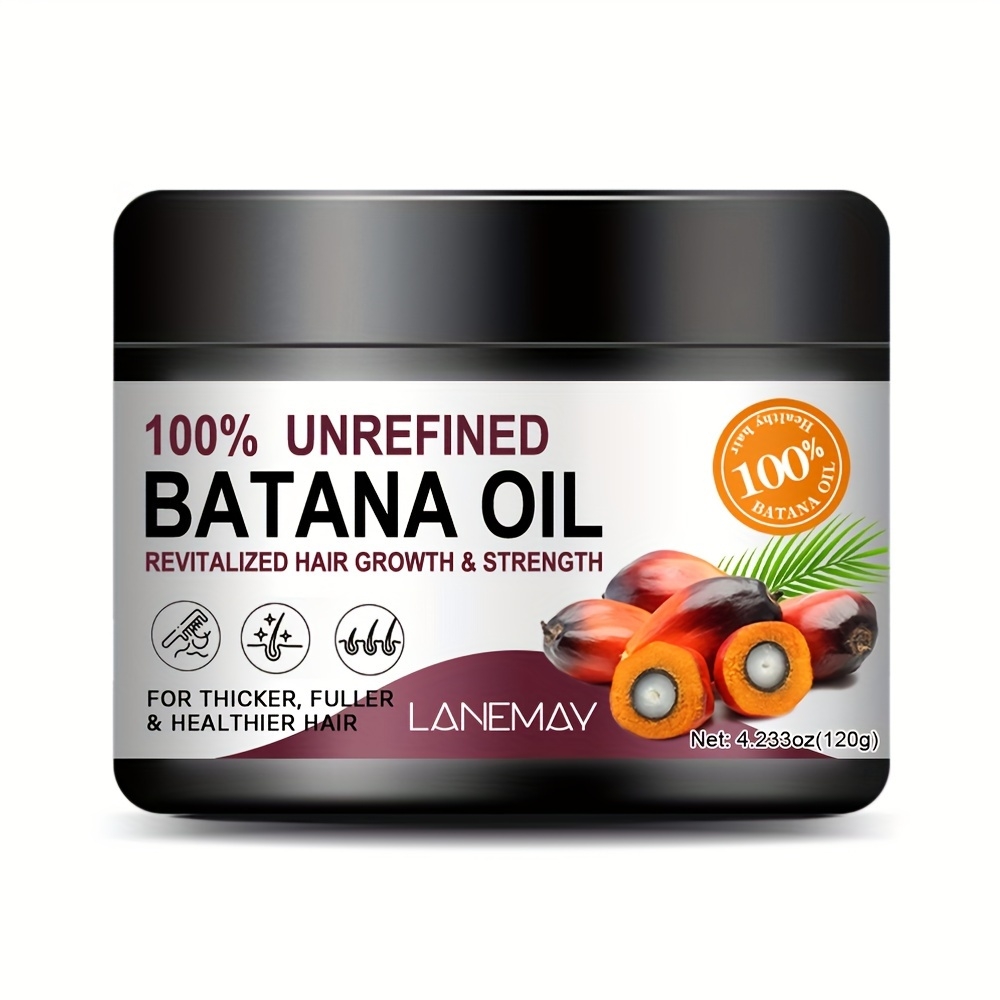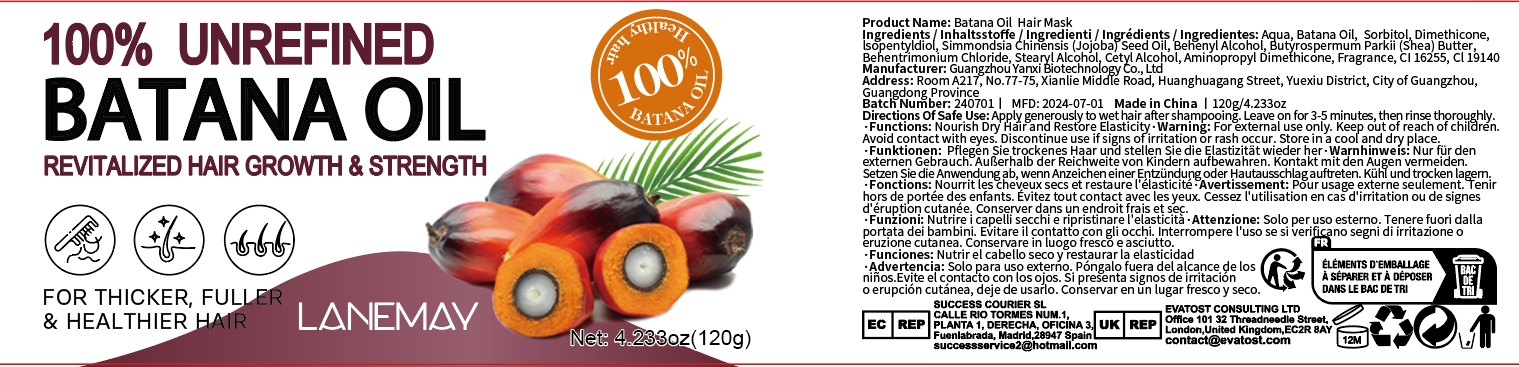 DRUG LABEL: Batana Oil Mask
NDC: 84025-151 | Form: CREAM
Manufacturer: Guangzhou Yanxi Biotechnology Co.. Ltd
Category: otc | Type: HUMAN OTC DRUG LABEL
Date: 20240816

ACTIVE INGREDIENTS: ISOPENTYLDIOL 3 mg/120 g; DIMETHICONE 5 mg/120 g
INACTIVE INGREDIENTS: WATER

DOSAGE AND ADMINISTRATION

Hair mask for moisturizing scalp and smoothing hair

WARNINGS

Keep out of children

INACTIVE INGREDIENT

Aqua

Keep out of children

INDICATIONS AND USAGE

For daily hair and scalp care

PURPOSE

Improve hair loss problems and promote hair growth